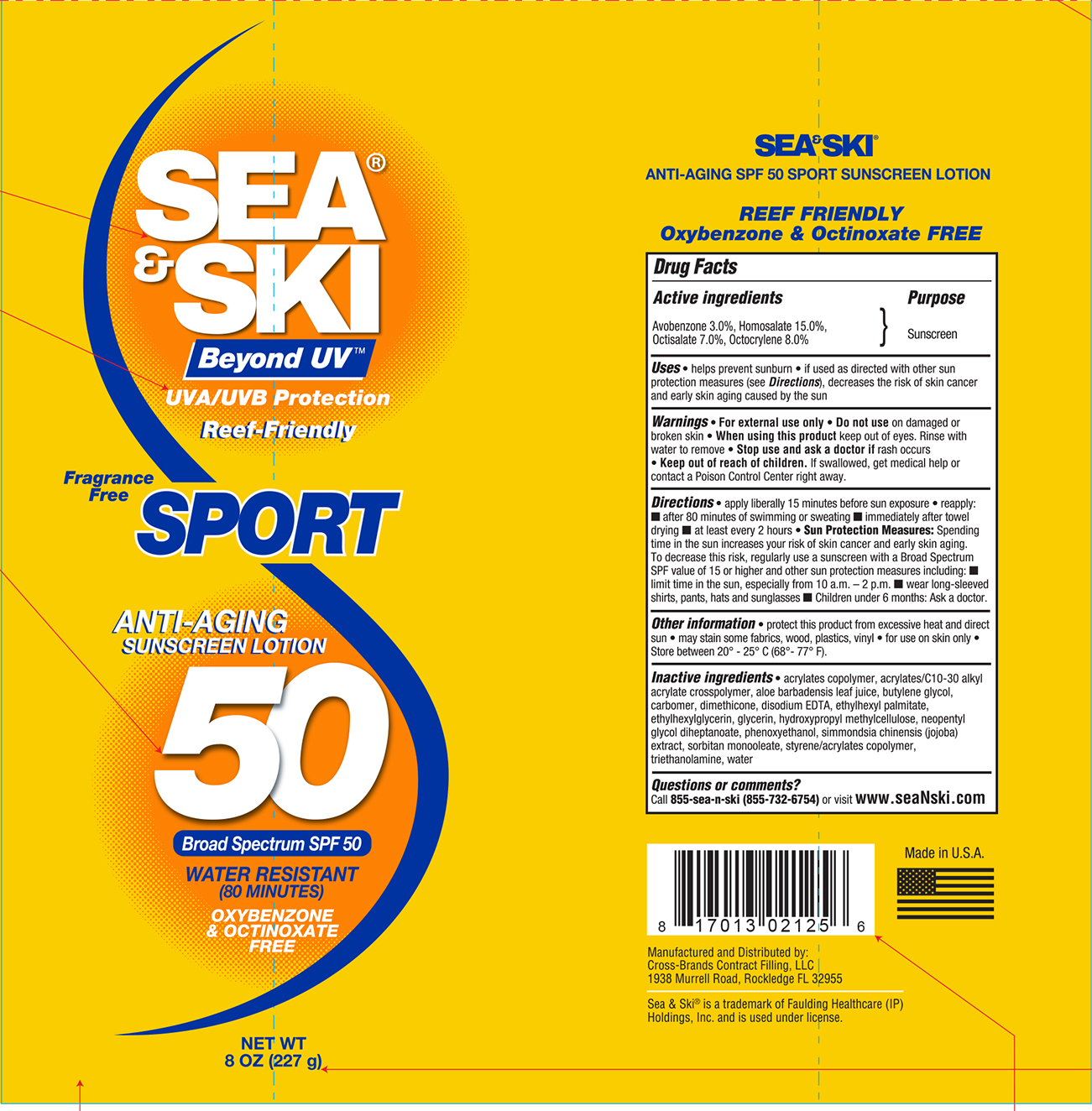 DRUG LABEL: Sea and Ski SPF 50 Sport
NDC: 73440-2125 | Form: LOTION
Manufacturer: Cross-Brands Contract Filling
Category: otc | Type: HUMAN OTC DRUG LABEL
Date: 20210219

ACTIVE INGREDIENTS: AVOBENZONE 6.81 g/227 g; HOMOSALATE 34.05 g/227 g; OCTOCRYLENE 18.16 g/227 g; OCTISALATE 15.89 g/227 g
INACTIVE INGREDIENTS: WATER 110 g/227 g

Sea&Ski SPF 50 Sport 8oz